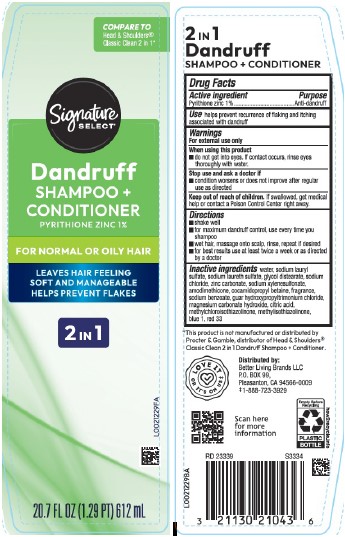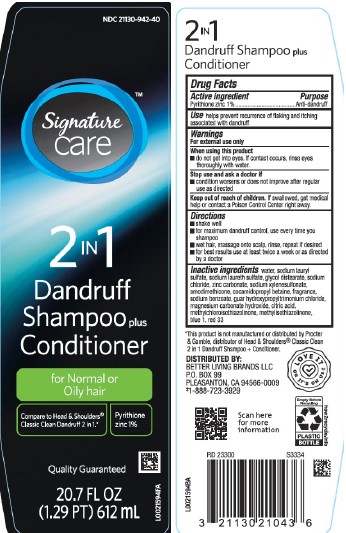 DRUG LABEL: 2 in 1 Dandruff
NDC: 21130-942 | Form: SHAMPOO
Manufacturer: Better Living Brands, LLC
Category: otc | Type: HUMAN OTC DRUG LABEL
Date: 20260223

ACTIVE INGREDIENTS: PYRITHIONE ZINC 10 mg/1 mL
INACTIVE INGREDIENTS: WATER; SODIUM LAURYL SULFATE; SODIUM LAURETH SULFATE; GLYCOL DISTEARATE; SODIUM CHLORIDE; ZINC CARBONATE; SODIUM XYLENESULFONATE; AMODIMETHICONE (800 CST); COCAMIDOPROPYL BETAINE; SODIUM BENZOATE; GUAR HYDROXYPROPYLTRIMONIUM CHLORIDE (1.7 SUBSTITUENTS PER SACCHARIDE); MAGNESIUM CARBONATE HYDROXIDE; CITRIC ACID MONOHYDRATE; METHYLCHLOROISOTHIAZOLINONE; METHYLISOTHIAZOLINONE; FD&C BLUE NO. 1; D&C RED NO. 33

Signature Care_Signature Select 311.007/311AK-AN
Everyday Clean 2 in 1 Dandruff Shampoo

Claims

2 in 1

Dandruff

Shampoo + Conditioner

Active ingredient

Pyrithione zinc 1%

Purpose

Anti-dandruff

Use

helps prevent recurrence of flaking and itching associated with dandruff

Warnings

For external use only

When using this product

- do not get into eyes. If contact occurs, rinse eyes thoroughly with water.

Stop use and ask a doctor if

- condition worsens or does not improve after regular use as directed

Keep out of reach of children.

If swallowed, get medical help or contact a Poison Control Center right away.

Directions

- shake well
- for maximum dandruff control, use every time you shampoo
- wet hair, massage onto scalp, rinse, repeat if desired
- for best results use at least twice a week or as directed by a doctor

inactive ingredients

water, sodium lauryl sulfate, sodium laureth sulfate, glycol distearate, sodium chloride, zinc carbonate, sodium xylenesulfonate, amodimethicone, cocamidopropyl betaine, fragrance, sodium benzoate, guar hydroxypropyltrimonium chloride, magnesium carbonate hydroxide, citric acid, methylchloroisothiazolinone, methylisothiazolinone, blue 1, red 33

Disclaimer

*This product is not manufactured or distributed by Procter & Gamble, distributor of Head & ShouldersClassic Clean 2 in 1 Dandruff Shampoo + Conditioner.

Adverse Reactions

DISTRIBUTED BY BETTER LIVING BRANDS LLC

P.O. BOX 99

PLEASANTON, CA 94566-0009

‡1-888-723-3929

LOVE IT OR IT'S ON US‡

Scan here for more information

Empty Before Recycling

PLASTIC BOTTLE

how2recycle.info

Principal display panel

NDC 21130-942-40

Signature Care™

2 in 1

Dandruff Shampoo plus Conditioner

for Normal or Oily hair

Compare to Head & Shoulders®Classic Clean Dandruff 2 in 1.*

Pyrithione zinc 1%

Quality Guaranteed

20.7 FL OZ (1.29 PT) 612 mL

PRINCIPAL DISPLAY PANEL

COMPARE TO Head & Shoulders®Classic Clean 2 in 1*

Signature SELECT®

Dandruff SHAMPOO + CONDITIONER

PYRITHIONE ZINC 1%

FOR NORMAL OR OILY HAIR

LEAVES HAIR FEELING SOFT AND MANAGEABLE

HELPS PREVENT FLAKES

2 IN 1

20.7 FL OZ (1.29 PT) 612 mL